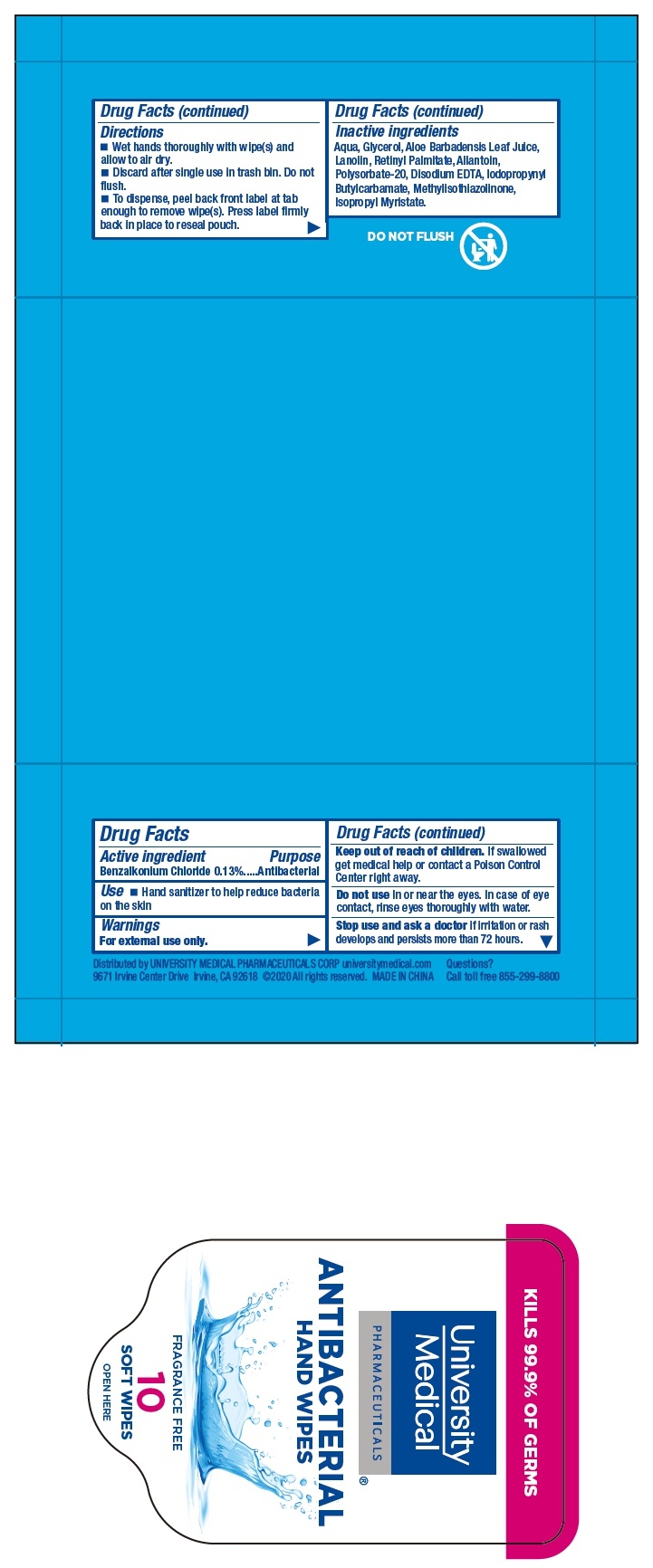 DRUG LABEL: University Medical Pharmaceuticals ANTIBACTERIAL HAND WIPES
NDC: 75127-003 | Form: CLOTH
Manufacturer: Jurong Dongfa General Merchandise Co Ltd
Category: otc | Type: HUMAN OTC DRUG LABEL
Date: 20220224

ACTIVE INGREDIENTS: BENZALKONIUM CHLORIDE 0.13 g/100 g
INACTIVE INGREDIENTS: IODOPROPYNYL BUTYLCARBAMATE; METHYLISOTHIAZOLINONE; POLYSORBATE 20; LANOLIN; ALOE VERA LEAF; ALLANTOIN; VITAMIN A PALMITATE; EDETATE DISODIUM ANHYDROUS; GLYCERIN; ISOPROPYL MYRISTATE; WATER

75127-003 University Medical Pharmaceuticals ANTIBACTERIAL HAND WIPES 0.13% Benzalkonium Chloride

Active Ingredient

Benzalkonium Chloride 0.13%

Purpose

Antibacterial

USE

hand sanitizer to help reduce bacteria on the skin.

Warning

For external use only.
Do not use In or near the eyes In case of eye
contact ,rinse eyes thoroughly with water.
Stop use and ask a doctor If Irritation or rash
develops and persists more than 72 hours.

●Keep out of reach of children unless under adult supervision.

Directions

Wet hands thoroughly with wipe(s) and
allow to air dry.
Discard after single use in trash bin. Do not
flush.
To dispense peel back front label at tab
enough to remove wipe(s)Press label firmly
back In place to reseal pouch.

Inactive ingredients

Aqua, Glycerol, Aloe Barbadensis Leaf Juice,
lanolin, Retinyl Palmitate, Allantoin,
Polysorbate-20, Disodium EDTA, lodopropynyl
Butylcarbamate , Methylisothlazollnone ,
lsopropyl Myristate.